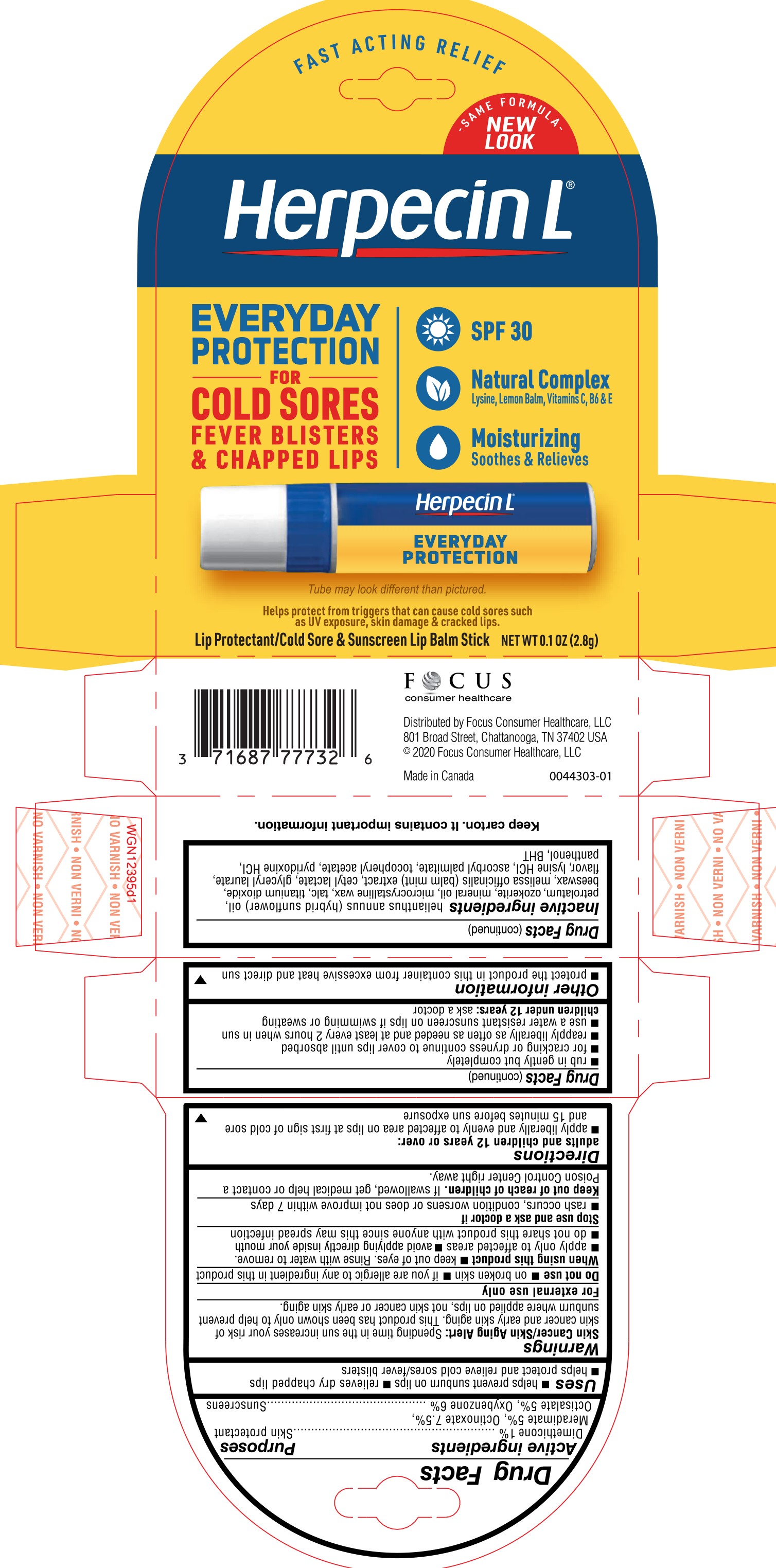 DRUG LABEL: Herpecin L
NDC: 71687-7773 | Form: STICK
Manufacturer: Focus Consumer Healthcare, LLC
Category: otc | Type: HUMAN OTC DRUG LABEL
Date: 20240131

ACTIVE INGREDIENTS: DIMETHICONE 1 g/100 g; MERADIMATE 5 g/100 g; OCTINOXATE 7.5 g/100 g; OCTISALATE 5 g/100 g; OXYBENZONE 6 g/100 g
INACTIVE INGREDIENTS: HELIANTHUS ANNUUS FLOWERING TOP; PETROLATUM; CERESIN; MINERAL OIL; MICROCRYSTALLINE WAX; TALC; TITANIUM DIOXIDE; APIS MELLIFERA; MELISSA OFFICINALIS; CETYL LACTATE; GLYCERYL LAURATE; LYSINE HYDROCHLORIDE; ASCORBYL PALMITATE; .ALPHA.-TOCOPHEROL ACETATE; PYRIDOXINE HYDROCHLORIDE; PANTHENOL; BUTYLATED HYDROXYTOLUENE

Herpecin L

PURPOSE

Skin protectant....Sunscreen

ACTIVE INGREDIENT

Dimethicone 1%

Meradimate 5%

Octinoxate 7.5%

Octisalate 5%

Oxybenzone 6%

Uses

- helps prevent sunburn on lips
- relieves dry chapped lips
- helps treat and relieve cold sores/fever blisters

Warnings

Skin Cancer/Skin Aging Alert: Spending time in the sun increases your risk of skin cancer and early skin aging. This product has been shown only to help prevent sunburn where applied on lips, not skin cancer or early skin aging.

Do not use

- on broken skin
- if you are allergic to any ingredient in this product

When using this product

- keep out of eyes. Rinse with water to remove.
- apply only to affected areas
- avoid applying directly inside your mouth
- do not share this product with anyone since this may spread infection

Stop use and ask a doctor if

- rash occurs, condition worsens or does not improve within 7 days

Keep out of reach of children.

If swallowed, get medical help or contact a Poison Control Center right away.

Directions

adults and children 12 years or over:

- apply liberally and evenly to affected area on lips at first sign of cold sore and 15 minutes before sun exposure
- rub in gently but completely
- for cracking or dryness continue to cover lips until absorbed
- reapply liberally as often as needed and at least every 2 hours when in sun
- use a water resistant sunscreen on lips if swimming or sweating

children under 12 years: ask a doctor

Other information

- protect the product in this container from excessive heat and direct sun

Inactive ingredients

helianthus annuus (hybrid sunflower) oil, petrolatum, ozokerite, mineral oil, microcrystalline wax, talc, titanium dioxide, beeswax, melissa officinalis (balm mint) extract, cetyl lactate, glyceryl laurate, flavor, lysine HCI, ascorbyl palmitate, tocopheryl acetate, pyridoxine HCI, panthenol, BHT

PACKAGE LABEL

Herpencin L

Everyday Protection for Cold Sores, Fever Blisters & Chapped Lips

SPF 30

Natural Complex

Moisturizing

Lip Protectant/Cold Sore & Sunscreen Lip Balm Stick NET WT 0.1 OZ (2.8 g)